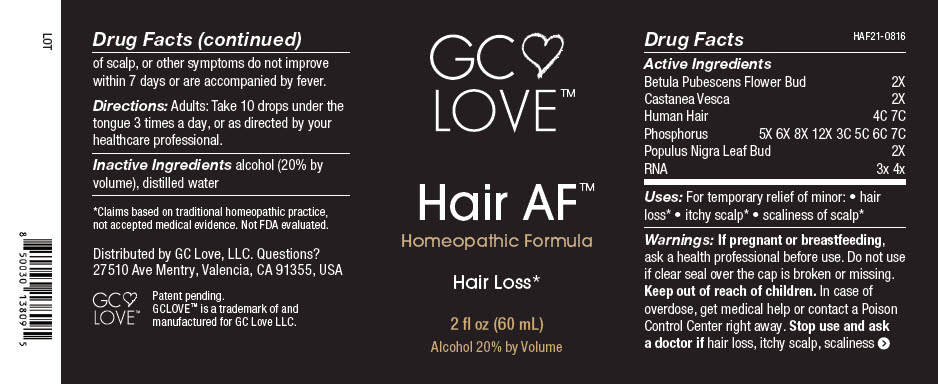 DRUG LABEL: Hair AF
NDC: 81812-0101 | Form: SOLUTION
Manufacturer: GC Love LLC
Category: homeopathic | Type: HUMAN OTC DRUG LABEL
Date: 20211022

ACTIVE INGREDIENTS: BETULA PUBESCENS FLOWER BUD 2 [hp_X]/1 mL; CASTANEA SATIVA LEAF 2 [hp_X]/1 mL; HUMAN HAIR 7 [hp_X]/1 mL; PHOSPHORUS 7 [hp_X]/1 mL; POPULUS NIGRA LEAF BUD 2 [hp_X]/1 mL; SACCHAROMYCES CEREVISIAE RNA 4 [hp_X]/1 mL
INACTIVE INGREDIENTS: ALCOHOL; WATER

Hair AF™

Drug Facts

Active Ingredients
Betula Pubescens Flower Bud | 2X
Castanea Vesca | 2X
Human Hair | 4C 7C
Phosphorus | 5X 6X 8X 12X 3C 5C 6C 7C
Populus Nigra Leaf Bud | 2X
RNA | 3x 4x

Uses

PURPOSE

For temporary relief of minor:

- hair loss [Claims based on traditional homeopathic practice, not accepted medical evidence. Not FDA evaluated.]
- itchy scalp
- scaliness of scalp

Warnings

PREGNANCY OR BREAST FEEDING

If pregnant or breastfeeding, ask a health professional before use. Do not use if clear seal over the cap is broken or missing.

Keep out of reach of children. In case of overdose, get medical help or contact a Poison Control Center right away.

Stop use and ask a doctor if hair loss, itchy scalp, scaliness of scalp, or other symptoms do not improve within 7 days or are accompanied by fever.

Directions

Adults: Take 10 drops under the tongue 3 times a day, or as directed by your healthcare professional.

Inactive Ingredients

alcohol (20% by volume), distilled water

Questions?

27510 Ave Mentry, Valencia, CA 91355, USA

Distributed by GC Love, LLC.

PRINCIPAL DISPLAY PANEL - 60 mL Bottle Label

GC
LOVE™

Hair AF™
Homeopathic Formula

Hair Loss*

2 fl oz (60 mL)
Alcohol 20% by Volume